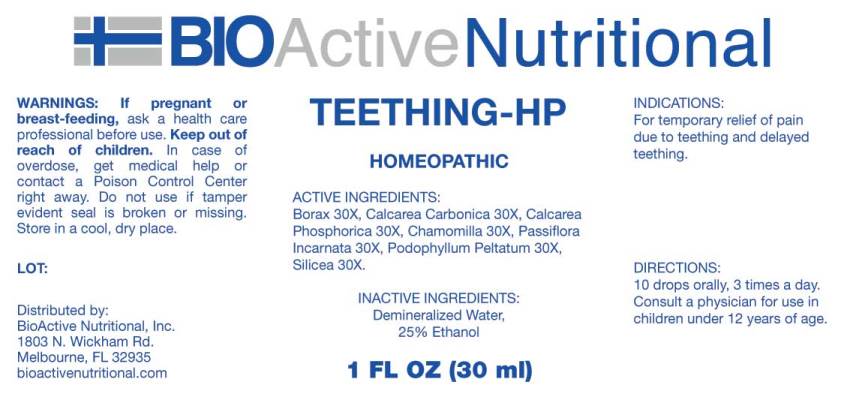 DRUG LABEL: Teething-HP
NDC: 43857-0447 | Form: LIQUID
Manufacturer: BioActive Nutritional, Inc.
Category: homeopathic | Type: HUMAN OTC DRUG LABEL
Date: 20170616

ACTIVE INGREDIENTS: SODIUM BORATE 30 [hp_X]/1 mL; OYSTER SHELL CALCIUM CARBONATE, CRUDE 30 [hp_X]/1 mL; TRIBASIC CALCIUM PHOSPHATE 30 [hp_X]/1 mL; MATRICARIA CHAMOMILLA 30 [hp_X]/1 mL; PASSIFLORA INCARNATA FLOWERING TOP 30 [hp_X]/1 mL; PODOPHYLLUM 30 [hp_X]/1 mL; SILICON DIOXIDE 30 [hp_X]/1 mL
INACTIVE INGREDIENTS: WATER; ALCOHOL

Drug Facts:

ACTIVE INGREDIENTS:

Borax 30X, Calcarea Carbonica 30X, Calcarea Phosphorica 30X, Chamomilla 30X, Passiflora Incarnata 30X, Podophyllum Peltatum 30X, Silicea 30X.

INDICATIONS:

For temporary relief of pain due to teething and delayed teething.

WARNINGS:

If pregnant or breast-feeding, ask a health care professional before use.

Keep out of reach of children. In case of overdose, get medical help or contact a Poison Control Center right away.

Do not use if tamper evident seal is broken or missing.

Store in cool, dry place.

Keep out of reach of children. In case of overdose, get medical help or contact a Poison Control Center right away.

DIRECTIONS:

10 drops orally, 3 times a day. Consult a physician for use in children under 12 years of age.

INDICATIONS:

For temporary relief of pain due to teething and delayed teething.

INACTIVE INGREDIENTS:

Demineralized Water, 25% Ethanol

QUESTIONS:

Distributed by:

BioActive Nutritional, Inc.

1803 N. Wickham Rd.

Melbourne, FL 32935

bioactivenutritional.com

PACKAGE LABEL DISPLAY:

BIOActive Nutritional

TEETHING-HP

HOMEOPATHIC

1 FL OZ (30 ml)